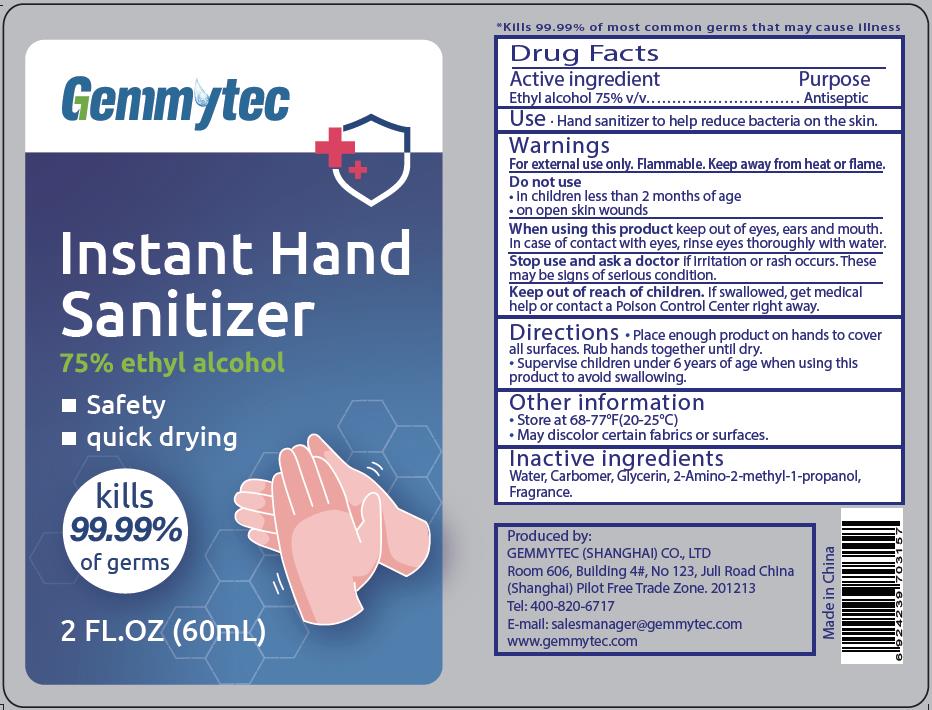 DRUG LABEL: Instant Hand Sanitizer
NDC: 81343-101 | Form: GEL
Manufacturer: Gemmytec (Shanghai) Co., Ltd
Category: otc | Type: HUMAN OTC DRUG LABEL
Date: 20201229

ACTIVE INGREDIENTS: ALCOHOL 45 mL/60 mL
INACTIVE INGREDIENTS: GLYCERIN; WATER; CARBOMER HOMOPOLYMER, UNSPECIFIED TYPE; LEMON OIL; AMINOMETHYLPROPANOL

Gemmytec EA 75% GEL 60mL

Active Ingredient(s)

Ethyl alcohol 75% v/v. Purpose: Antiseptic

Purpose

Antiseptic

Use

Hand sanitizer to help reduce bacteria on the skin.

Warnings

For external use only. Flammable. Keep away from heat or flame.

Do not use

- in children less than 2 months of age
- on open skin wounds

When using this product keep out of eyes, ears and mouth. If case of contact with eyes, rinse eyes thoroughly with water.

Stop use and ask a doctor if irritation or rash occurs. These may be signs of serious condition.

Keep out of reach of children. If swallowed, get medical help or contact a Poison Control Center right away.

Directions

- Place enough product on hands to cover all surfaces. Rub hands together until dry.
- Supervise children under 6 years of age when using this product to avoid swallowing.

Other information

- Store at 68-77℉(20-25℃).
- May discolor certain fabrics or surfaces.

Inactive ingredients

Water, Carbomer, Glycerin, 2-Amino-2-methyl-1-propanol, Fragrance.